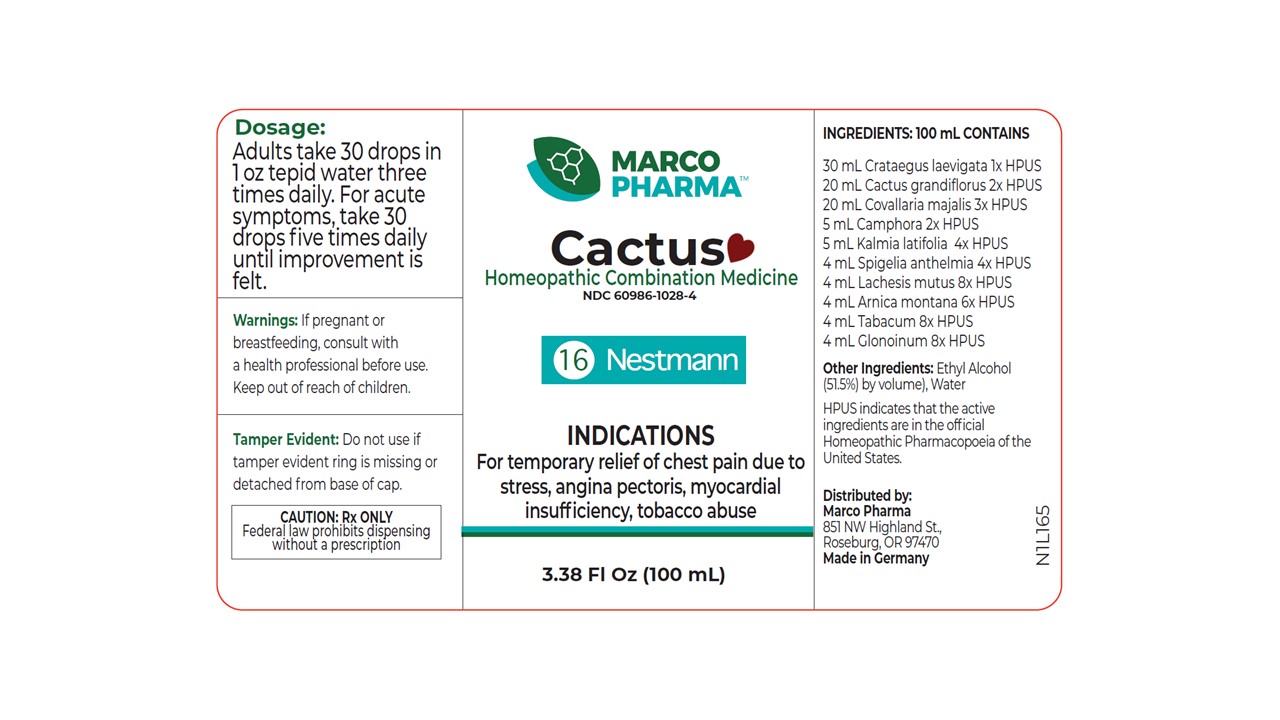 DRUG LABEL: CACTUS
NDC: 60986-1028 | Form: LIQUID
Manufacturer: Marco Pharma International LLC.
Category: homeopathic | Type: HUMAN PRESCRIPTION DRUG LABEL
Date: 20241204

ACTIVE INGREDIENTS: CAMPHOR (NATURAL) 2 [hp_X]/100 mL; KALMIA LATIFOLIA LEAF 4 [hp_X]/100 mL; SPIGELIA ANTHELMIA 4 [hp_X]/100 mL; LACHESIS MUTA VENOM 8 [hp_X]/100 mL; ARNICA MONTANA 6 [hp_X]/100 mL; TOBACCO LEAF 8 [hp_X]/100 mL; NITROGLYCERIN 8 [hp_X]/100 mL; SELENICEREUS GRANDIFLORUS STEM 2 [hp_X]/100 mL; CONVALLARIA MAJALIS 3 [hp_X]/100 mL; CRATAEGUS LAEVIGATA WHOLE 1 [hp_X]/100 mL
INACTIVE INGREDIENTS: ALCOHOL; WATER

Drug Facts

Active Ingredients

Midland Hathorne 1XHPUS

Night Blooming Cerus 2XHPUS

Lily of the Valley 3XHPUS

Natural Camphor 2XHPUS

Mountain laurel 4XHPUS

Pinkroot 4XHPUS

Bushmaster viper 8XHPUS

Mountain Arnica 6XHPUS

Tabacco 8XHPUS

Nitroglycerin 8XHPUS

The letters HPUS indicates that the components in this product are officially monographed in the Homeopathic Pharmacopoeia of United Sates.

Purpose

FOR RELIEF OF CHEST PAIN DUE TO STRESS; ANGINA PECTORIS; MYOCARDIAL INSUFFICIENCY; TOBACCO ABUSE.

Keep out of reach of children.

Dosage

Adults take 30 drops in 1 oz water three times daily. For acute symptoms, take 40 drops four to five times daily. Children receive 10 drops in 1 oz tepid water three time daily.

Warnings

If pregnant or breast-feeding, consult a health professional before use.

DOSAGE AND ADMINISTRATION

(Read Suggested Use Section)

Inactive Ingredients

CONTAINS E thyl Alcohol (51.5% by vol.) and Water